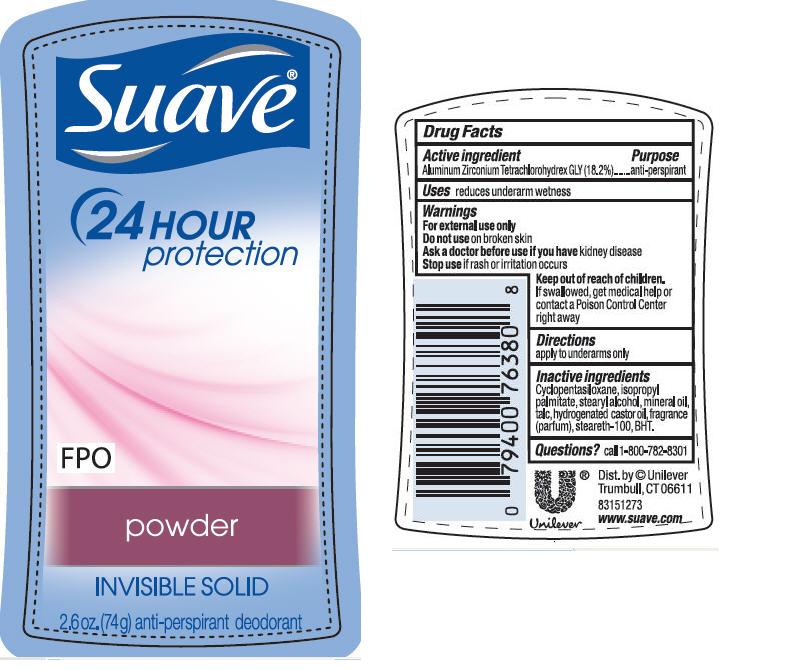 DRUG LABEL: Suave
NDC: 64942-1142 | Form: STICK
Manufacturer: Conopco Inc. d/b/a Unilever
Category: otc | Type: HUMAN OTC DRUG LABEL
Date: 20101202

ACTIVE INGREDIENTS: Aluminum Zirconium Tetrachlorohydrex GLY 18.2 g/100 g
INACTIVE INGREDIENTS: CYCLOMETHICONE 5; ISOPROPYL PALMITATE; Stearyl Alcohol; HYDROGENATED CASTOR OIL; TALC; MINERAL OIL; STEARETH-100; BUTYLATED HYDROXYTOLUENE

Suave IS Powder antiperspirant deodorant

Active Ingredient

Aluminum Zirconium Tetrachlorohydrex GLY (18.2%)

Purpose
anti-perspirant

INDICATIONS AND USAGE

Uses reduces underarm wetness

Warnings
For External Use Only

Do not use on broken skin

Ask a doctor before use if you have kidney disease

Stop use if rash or irritation occurs

Keep out of reach of children. If swallowed, get medical help or contact a Poison Control Center right away

DOSAGE AND ADMINISTRATION

Directions apply to underarms only

Inactive ingredients
Cyclopentasiloxane
Isopropyl Palmitate
Stearyl Alcohol
Mineral Oil
Talc
Hydrogenated Castor Oil
Fragrance (Parfum)
Steareth-100
BHT

Questions? Call 1-800-782-8301

PACKAGE LABEL

2.6 oz PDP